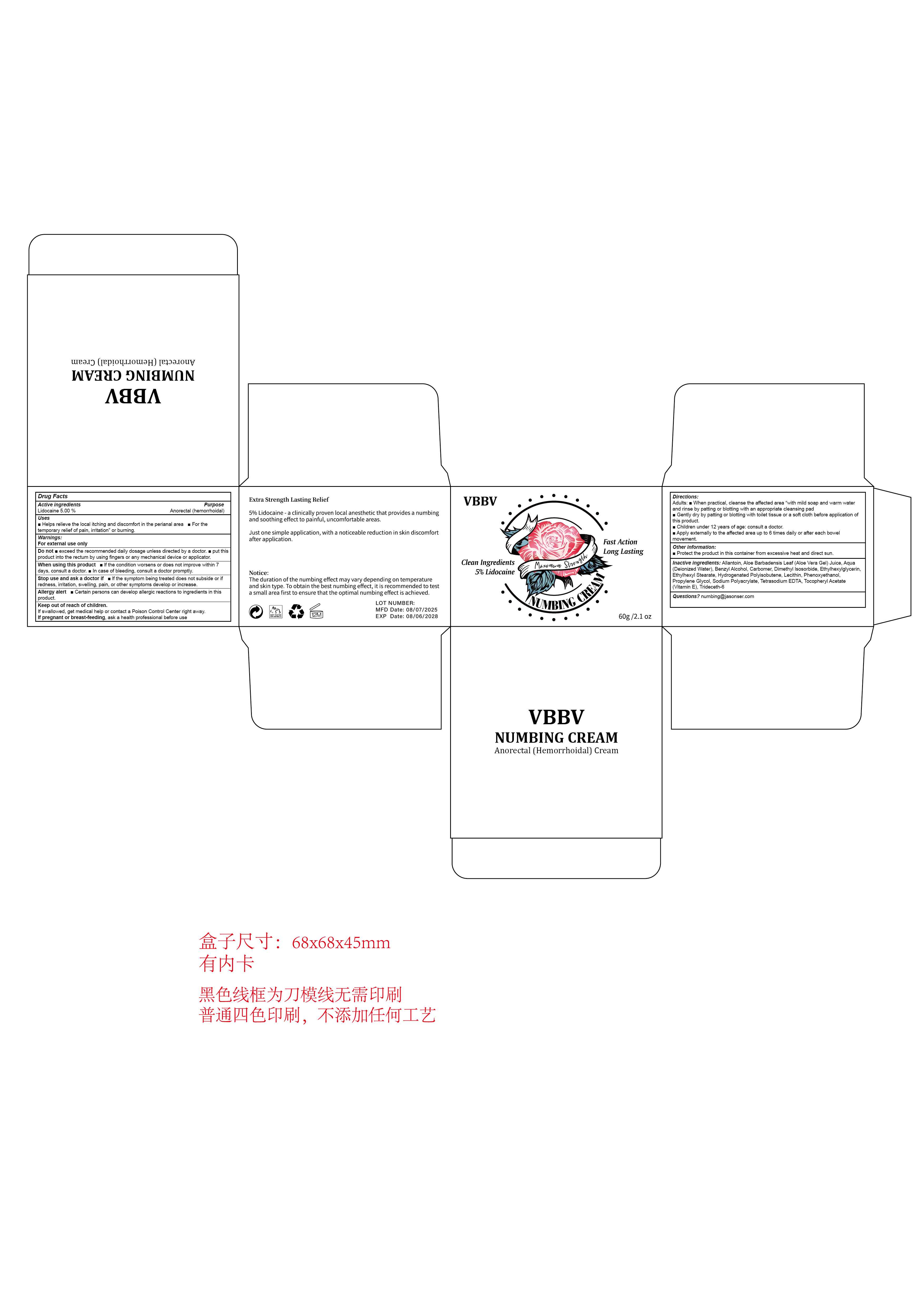 DRUG LABEL: VBBV Anorectal(Hemorrhoidal) Creams
NDC: 84867-020 | Form: CREAM
Manufacturer: Jiashen International Trading Co., Ltd.
Category: otc | Type: HUMAN OTC DRUG LABEL
Date: 20250819

ACTIVE INGREDIENTS: LIDOCAINE 5 g/100 mL
INACTIVE INGREDIENTS: PURSLANE; PEG-40 HYDROGENATED CASTOR OIL; PRILOCAINE; AQUA; PROPYLENE GLYCOL; CARBOMER; GLYCERIN; MENTHA ARVENSIS LEAF; CHRYSANTHELLUM INDICUM TOP; TETRACAINE; EDETATE DISODIUM; HYDROXYACETOPHENONE; 1,2-HEXANEDIOL

ACTIVE INGREDIENT

Lidocaine 5.00 %
Anorectal (hemorrhoidal)

PURPOSE

Helps relieve the local itching and discomfort in the perianal area m For thetemporary relief of pain, irritation" or burning.

Keep out of reach of children.
lf swallowed, get medical help or contact a Poison Control Center right away.If pregnant or breast-feeding, ask a health professional before use

Warnings:For external use only

When using this product m lf the condition worsens or does not improve within 7days, consult a doctor. m In case of bleeding, consult a doctor promptly.

Directions:
Adults: m When practical, cleanse the affected area “with mild soap and warm waterand rinse by patting or blotting with an appropriate cleansing padGently dry by patting or blotting with toilet tissue or a soft cloth before application ofthis product.
Children under 12 years of age: consult a doctor.Apply externally to the affected area up to 6 times daily or after each bowelmovement.

INACTIVE INGREDIENT

Inactive ingredients: Allantoin, Aloe Barbadensis Leaf (Aloe Vera Gel) Juice, Aqua(Deionized Water), Benzy Alcohol, Carbomer, Dimethyl lsosorbide, Ethylhexylglycerin,.Ethylhexyl Stearate, Hydrogenated Polyisobutene, Lecithin, Phenoxyethanol,Propylene Glycol, Sodium Polyacrylate, Tetrasodium EDTA, Tocopheryl Acetate(Vitamin E), Trideceth-6

Other information:Protect the product in this container from excessive heat and direct sun.